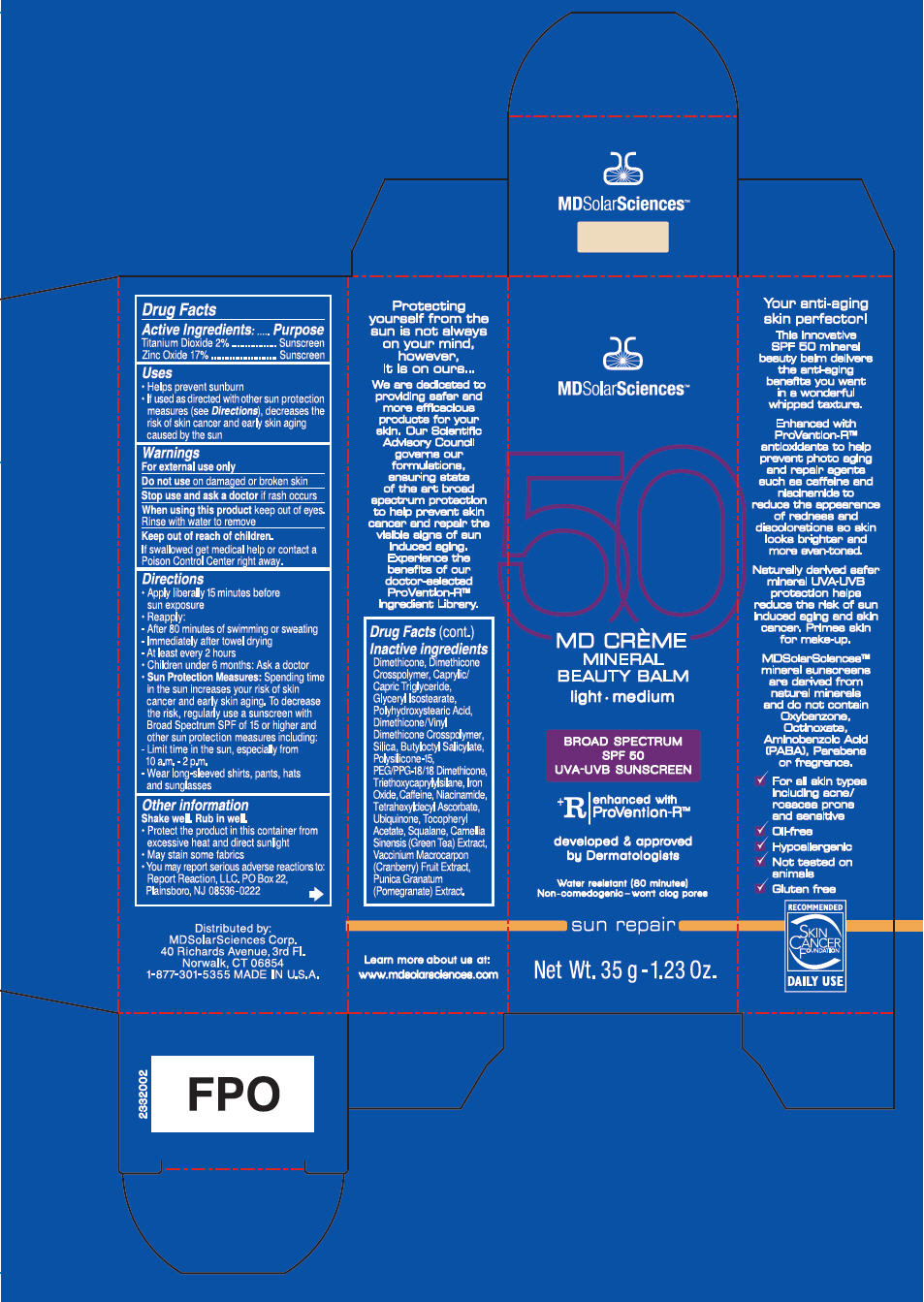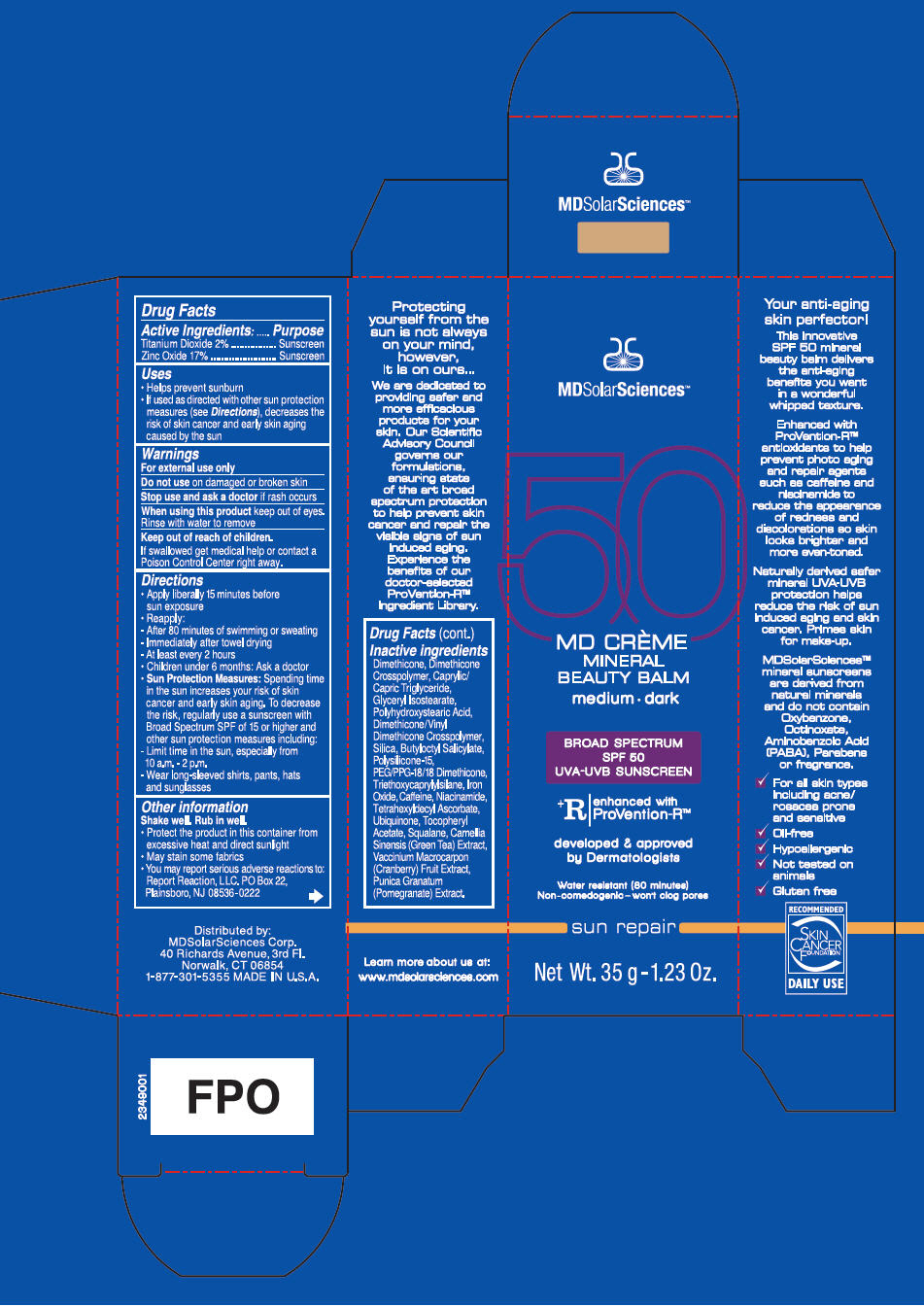 DRUG LABEL: Mineral Beauty Balm 
NDC: 49358-550 | Form: CREAM
Manufacturer: MDSolarSciences
Category: otc | Type: HUMAN OTC DRUG LABEL
Date: 20200127

ACTIVE INGREDIENTS: Titanium Dioxide 2.7 g/35 g; Zinc Oxide 1.3 g/35 g
INACTIVE INGREDIENTS: Dimethicone; DIMETHICONE/DIENE DIMETHICONE CROSSPOLYMER; MEDIUM-CHAIN TRIGLYCERIDES; GLYCERYL ISOSTEARATE; POLYHYDROXYSTEARIC ACID (2300 MW); DIMETHICONE/VINYL DIMETHICONE CROSSPOLYMER (SOFT PARTICLE); Silicon Dioxide; BUTYLOCTYL SALICYLATE; POLYSILICONE-15; TETRAHEXYLDECYL ASCORBATE; PEG/PPG-18/18 DIMETHICONE; TRIETHOXYCAPRYLYLSILANE; FERRIC OXIDE RED; CAFFEINE; NIACINAMIDE; UBIDECARENONE; .ALPHA.-TOCOPHEROL ACETATE; SQUALANE; GREEN TEA LEAF; CRANBERRY; POMEGRANATE JUICE

Mineral Beauty Balm
Broad Spectrum SPF 50 Sunscreen UVA-UVB Suncreen

Drug Facts

ACTIVE INGREDIENT

Active Ingredients | Purpose
Titanium Dioxide 2% | Sunscreen
Zinc Oxide 17% | Sunscreen

Uses

- Helps prevent sunburn
- If used as directed with other sun protection measures (see Directions), decreases the risk of skin cancer and early skin aging caused by the sun

Warnings

For external use only

Do not use on damaged or broken skin

Stop use and ask a doctor if rash occurs

When using this product keep out of eyes. Rinse with water to remove

Keep out of reach of children. If swallowed, get medical help or contact a Poison Control Center right away

Directions

- Apply liberally 15 minutes before sun exposure
- Reapply:
  After 80 minutes of swimming or sweating
  Immediately after towel drying
  At least every 2 hours
  Children under 6 months: Ask a doctor
- Sun Protection Measures: Spending time in the sun increases your risk of skin cancer and early skin aging. To decrease the risk, regularly use a sunscreen with Broad Spectrum SPF of 15 or higher and other sun protection measures including:
  - Limit time in the sun, especially from 10 a.m. – 2 p.m.
  - Wear long-sleeved shirts, pants, hats and sunglasses

Other Information

- Shake well. Rub in well.
- Protect the product in this container from excessive heat and direct sunlight
- May stain some fabrics
- You may report serious adverse reaction to: Report Reaction, LLC. PO Box 22, Plainsboro, NJ 08536-0222

Inactive Ingredients

Dimethicone, Dimethicone Crosspolymer, Caprylic/Capric Triglyceride, Glyceryl Isostearate, Polyhydroxystearic Acid, Dimethicone/Vinyl Dimethicone Crosspolymer, Silica, Butyloctyl Salicylate, Polysilicone-15, Tetrahexyldecyl Ascorbate, PEG/PPG-18/18 Dimethicone, Triethoxycaprylylsilane, Iron Oxide, Caffeine, Niacinamide, Ubiquinone, Tocopheryl Acetate, Squalane, Camellia Sinensis (Green Tea) Extract, Vaccinium Macrocarpon (Cranberry) Fruit Extract, Punica Granatum (Pomegranate) Extract.

PRINCIPAL DISPLAY PANEL - 35 g Tube Carton - Light/Medium

MDSolarSciences™

50

MD CRÈME
MINERAL
BEAUTY BALM

light • medium

BROAD SPECTRUM
SPF 50
UVA-UVB SUNSCREEN

^+ R
enhanced with
ProVention-R™

developed & approved
by Dermatologists

Water resistant (80 minutes)
Non-comedogenic – won't clog pores

sun repair

Net Wt. 35 g - 1.23 Oz.

PRINCIPAL DISPLAY PANEL - 35 g Tube Carton - Medium/Dark

MDSolarSciences™

50

MD CRÈME
MINERAL
BEAUTY BALM

medium • dark

BROAD SPECTRUM
SPF 50
UVA-UVB SUNSCREEN

^+ R
enhanced with
ProVention-R™

developed & approved
by Dermatologists

Water resistant (80 minutes)
Non-comedogenic – won't clog pores

sun repair

Net Wt. 35 g - 1.23 Oz.